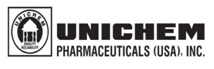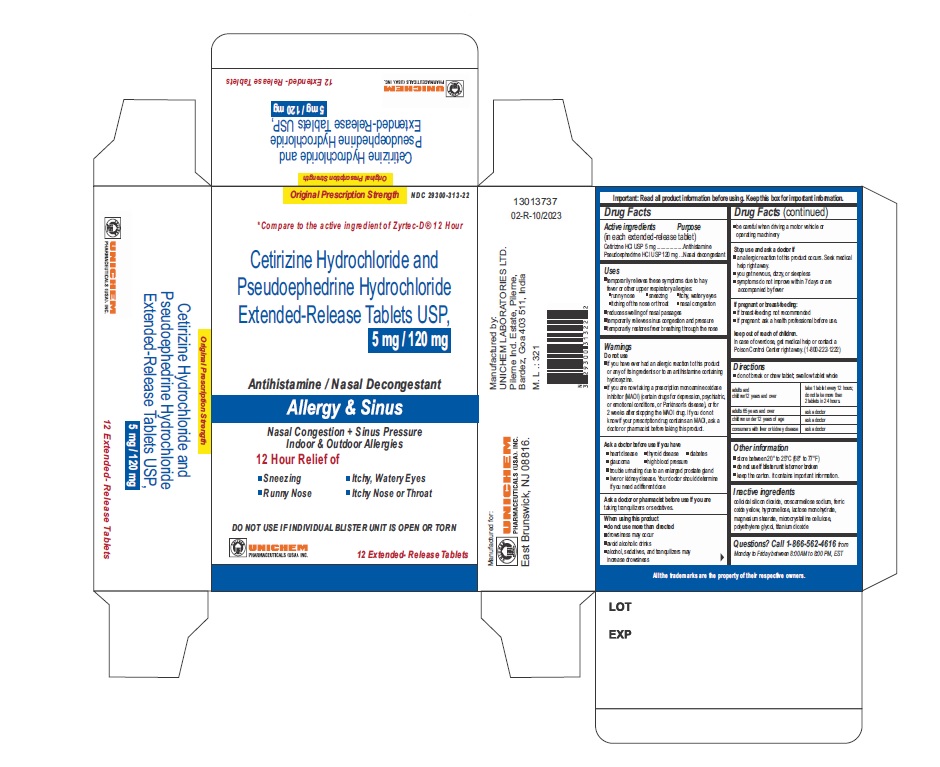 DRUG LABEL: Cetirizine Hydrochloride and Pseudoephedrine Hydrochloride
NDC: 29300-313 | Form: TABLET, FILM COATED, EXTENDED RELEASE
Manufacturer: Unichem Pharmaceuticals (USA), Inc.
Category: otc | Type: HUMAN OTC DRUG LABEL
Date: 20240923

ACTIVE INGREDIENTS: CETIRIZINE HYDROCHLORIDE 5 mg/1 1; PSEUDOEPHEDRINE HYDROCHLORIDE 120 mg/1 1
INACTIVE INGREDIENTS: CELLULOSE, MICROCRYSTALLINE; CROSCARMELLOSE SODIUM; FERRIC OXIDE YELLOW; HYPROMELLOSE 2208 (100000 MPA.S); HYPROMELLOSE 2208 (4000 MPA.S); HYPROMELLOSE 2910 (5 MPA.S); LACTOSE MONOHYDRATE; MAGNESIUM STEARATE; POLYETHYLENE GLYCOL 400; SILICON DIOXIDE; TITANIUM DIOXIDE

CETIRIZINE HYDROCHLORIDE AND PSEUDOEPHEDRINE HYDROCHLORIDE extended-release tablets, USP
ALLERGY AND CONGESTION

DRUG FACTS

ACTIVE INGREDIENTS

(in each extended-release tablet)

Cetirizine HCl USP 5 mg

Pseudoephedrine HCl USP 120 mg

Antihistamine

Nasal decongestant

USES

- temporarily relieves these symptoms due to hay fever or other upper respiratory allergies:
  - runny nose
  - sneezing
  - itchy, watery eyes
  - itching of the nose or throat
  - nasal congestion
- reduces swelling of nasal passages
- temporarily relieves sinus congestion and pressure
- temporarily restores freer breathing through the nose

WARNINGS

Do Not Use

- if you have ever had an allergic reaction to this product or any of its ingredients or to an antihistamine containing hydroxyzine.
- if you are now taking a prescription monoamine oxidase inhibitor (MAOI) (certain drugs for depression, psychiatric, or emotional conditions, or Parkinson's disease), or for 2 weeks after stopping the MAOI drug. If you do not know if your prescription drug contains an MAOI, ask a doctor or pharmacist before taking this product.

Ask a doctor before use if you have

- heart disease
- thyroid disease
- diabetes
- glaucoma
- high blood pressure
- trouble urinating due to an enlarged prostate gland
- liver or kidney disease. Your doctor should determine if you need a different dose.

When using this product

- do not use more than directed
- drowsiness may occur
- avoid alcoholic drinks
- alcohol, sedatives, and tranquilizers may increase drowsiness
- be careful when driving a motor vehicle or operating machinery

Stop use and ask doctor if

- an allergic reaction to this product occurs. Seek medical help right away.
- you get nervous, dizzy, or sleepless
- symptoms do not improve within 7 days or are accompanied by fever

If pregnant or breast-feeding:

- if breast-feeding: not recommended
- if pregnant: ask a health professional before use.

Keep out of reach of children

In case of overdose, get medical help or contact a Poison Control Center right away. (1-800-222-1222)

DIRECTIONS

- do not break or chew tablet; swallow tablet whole

adults and children 12 years and over | take 1 tablet every 12 hours; do not take more than 2 tablets in 24 hours
adults 65 years and over | ask a doctor
children under 12 years of age | ask a doctor
consumers with liver or kidney disease | ask a doctor

OTHER INFORMATION

- store between 20° to 25°C (68° to 77°F)
- do not use if blister unit is torn or broken
- keep the carton. It contains important information.

colloidal silicon dioxide, croscarmellose sodium, ferric oxide yellow, hypromellose, lactose monohydrate, magnesium stearate, microcrystalline cellulose, polyethylene glycol, titanium dioxide

call 1-866-562-4616 from Monday to Friday between 8.00 AM to 8.00 PM, EST

Manufactured by:

UNICHEM LABORATORIES LTD.

Pilerne Ind. Estate, Pilerne, Bardez,

Goa 403511, India.

Manufactured for:

East Brunswick, NJ 08816.